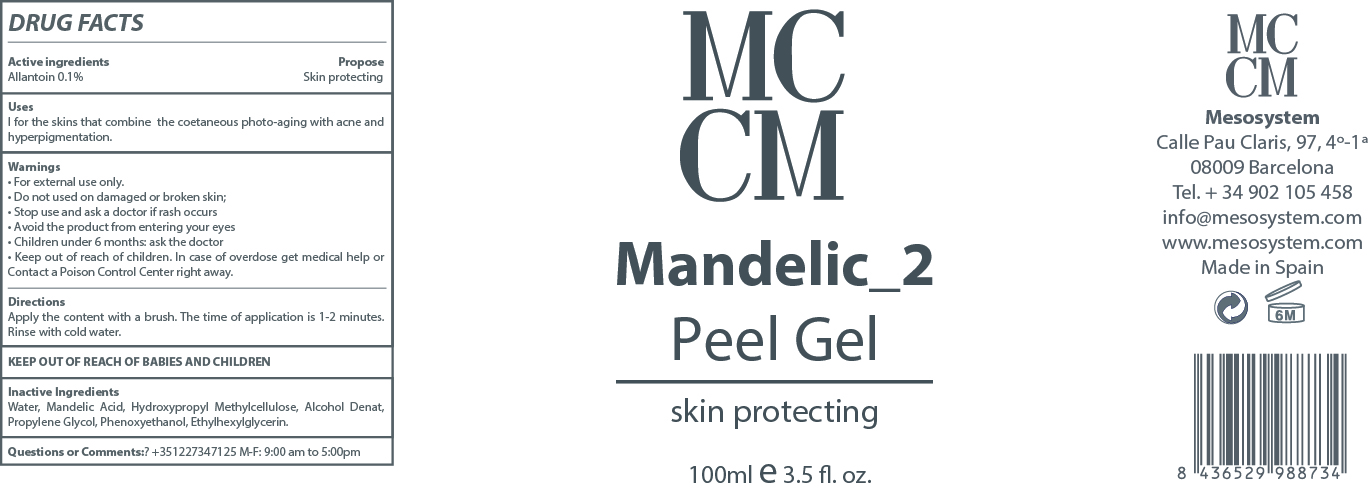 DRUG LABEL: Salicylic 2 Peel Gel
NDC: 70663-012 | Form: GEL
Manufacturer: MESO SYSTEM S.A.
Category: otc | Type: HUMAN OTC DRUG LABEL
Date: 20171102

ACTIVE INGREDIENTS: ALLANTOIN 0.1 mg/1 mL
INACTIVE INGREDIENTS: HYDROXYETHYL ETHYLCELLULOSE 2 mg/1 mL; WATER 69.9 mg/1 mL; SALICYLIC ACID 2 mg/1 mL; PHENOXYETHANOL 0.9 mg/1 mL; ETHYLHEXYLGLYCERIN 0.1 mg/1 mL; PROPANEDIOL 10 mg/1 mL; ALCOHOL 1.5 mg/1 mL

Salicylic 2 Peel Gel

Warnings

Stop use and ask a Doctor if rash occurs

WARNINGS

- For external use only.
- Do no use on damaged or broken skin
- Stop use and ask a doctor if rash occurs
- Avoid the product from entering your eyes
- Children under 6 months Ask a Doctor

USES

- Is for the skin that combines the coetaneus photo aging with acne and hyperpigmentation.

- Keep out of the reach of chuldren.
- In case of overdose get medical help or Contact a Poison Control Center right away.

DIRECTIONS

Apply the content with a brush. The time of application is 1 to 2 minutes. Rinse with cold water.

QUESTIONS OR COMMENTS ?

- +35 1227347125 M-F: 9:00 am to 5:00 pm

ACTIVE INGREDIENTS

Active Ingredients Purpose

Allantoin 0.1%...................................................................................................................................................Skin Protectant

Inactive Ingredients

water, mandelic acid, hydroxyethyl ethylcellulose, alcohol denat, propanediol, phenoxyethanol, ethylhexylglycerin

INDICATIONS AND USAGE

Is for the skin that combines the coetaneus photo aging with acne and hyperpigmentation.

Mandelic_2 Peel Gel

Skin Protecting